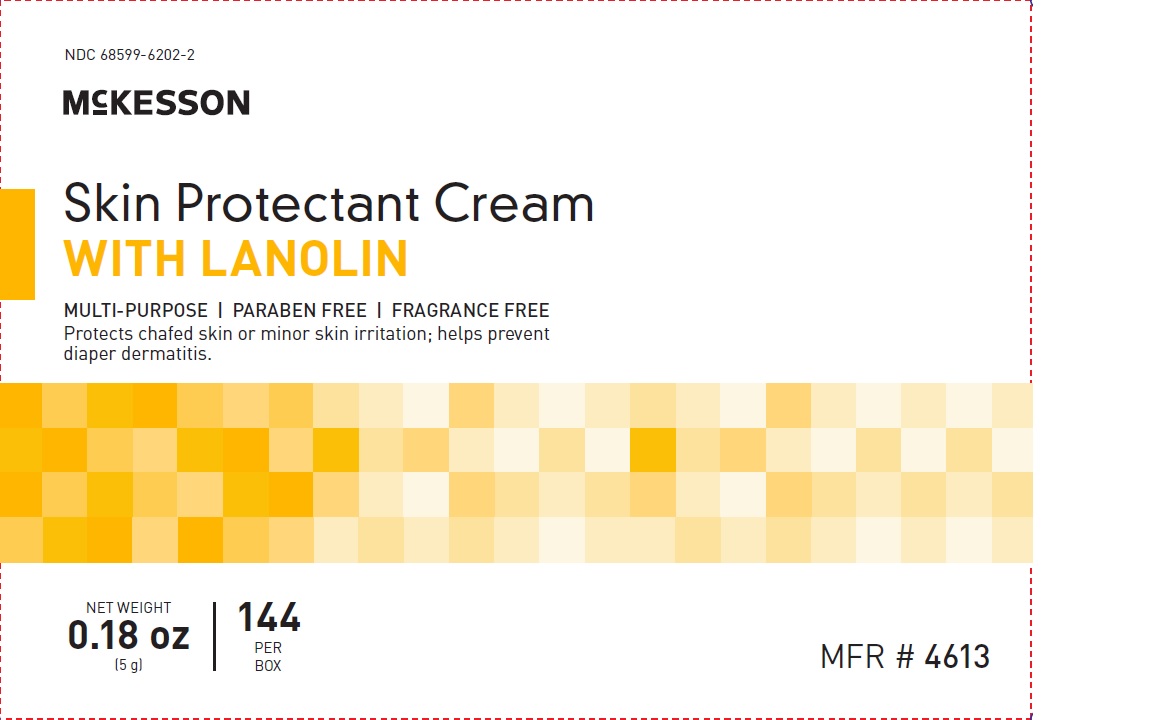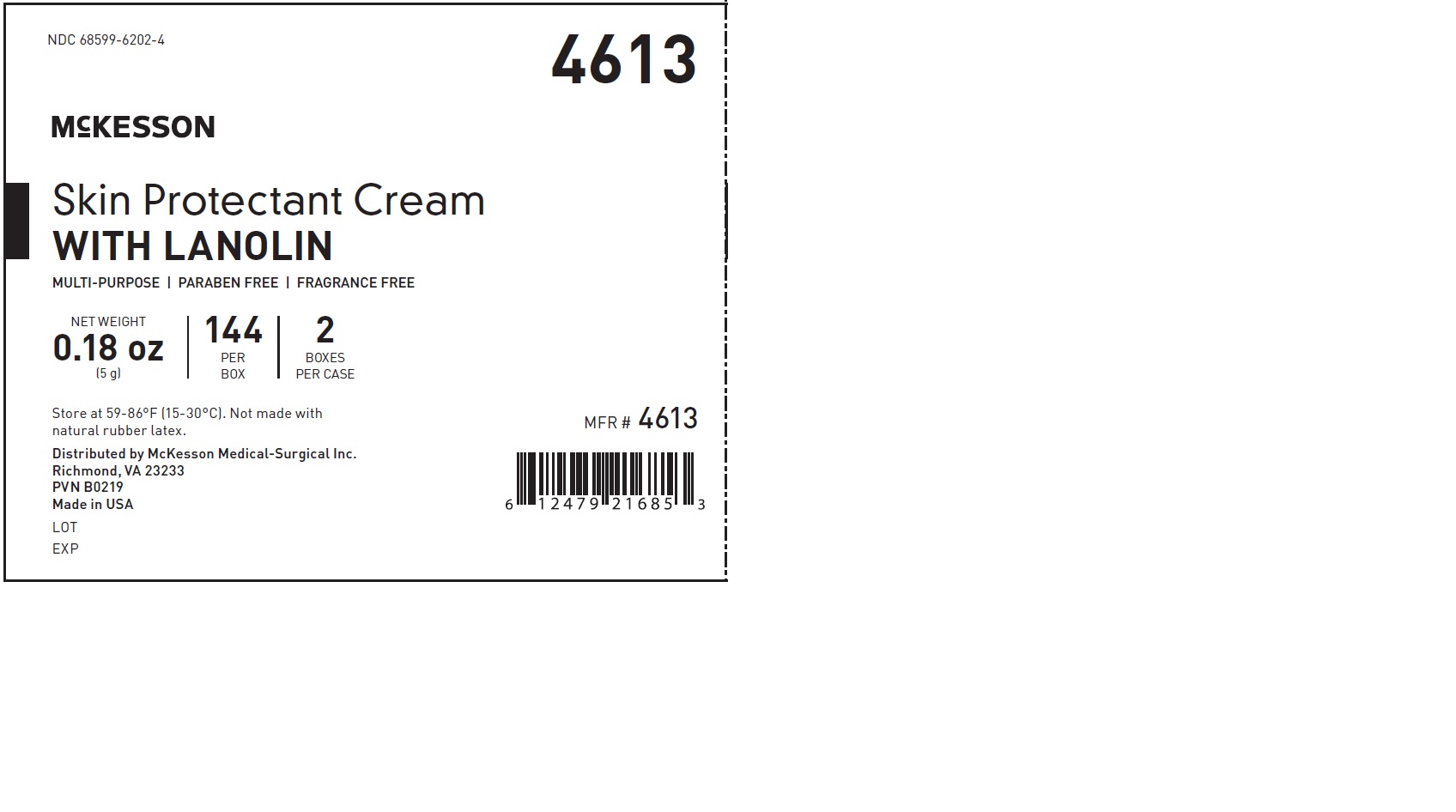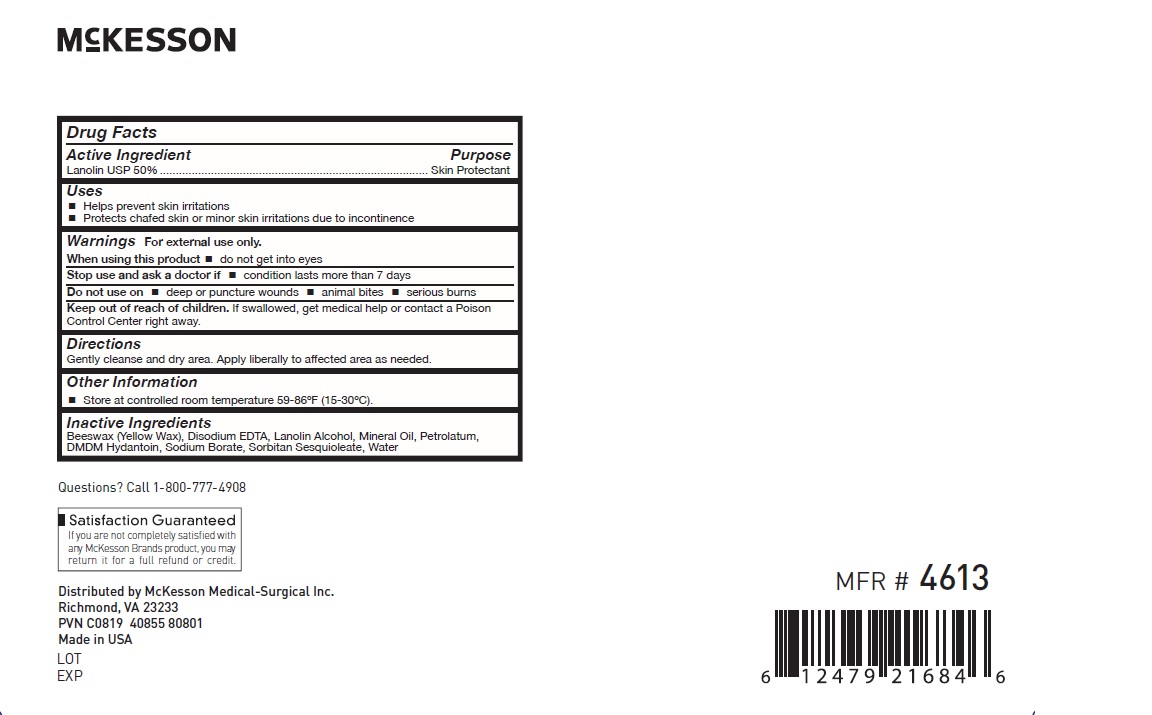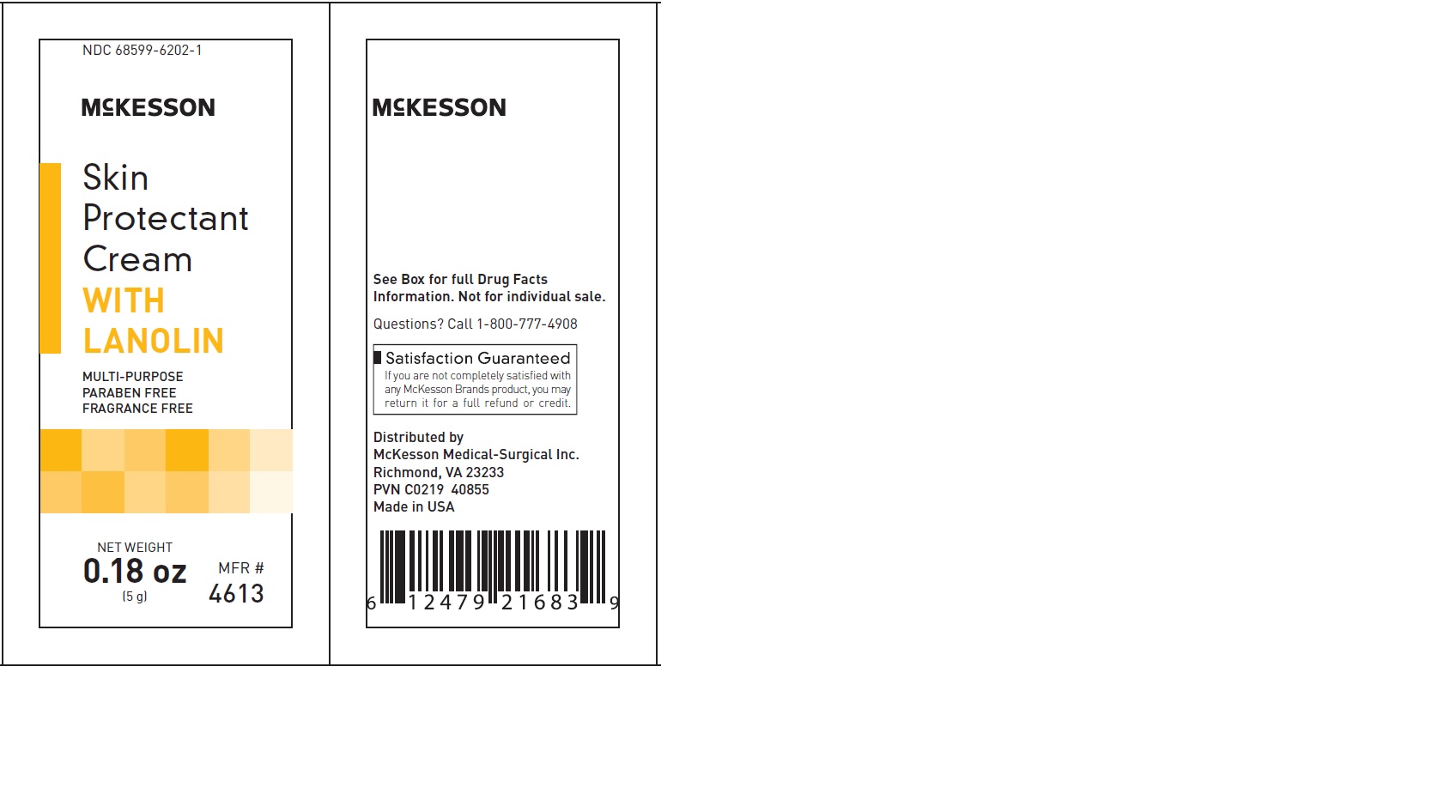 DRUG LABEL: Skin Protectant with Lanolin
NDC: 68599-6202 | Form: CREAM
Manufacturer: McKesson Medical-Surgical Inc.
Category: otc | Type: HUMAN OTC DRUG LABEL
Date: 20241014

ACTIVE INGREDIENTS: LANOLIN 50 g/100 g
INACTIVE INGREDIENTS: DISODIUM EDTA-COPPER; LANOLIN ALCOHOLS; DMDM HYDANTOIN; SODIUM BORATE; SORBITAN SESQUIOLEATE; WATER; YELLOW WAX; MINERAL OIL; ALOE

4613

ACTIVE INGREDIENT

Lanolin 50%

Purpose: Skin protectant

INDICATIONS AND USAGE

Temporarily protects minor cuts, scrapes and burns

Temporarily protects and helps relieve chafed, chapped or cracked skin and lips

Helps prevent incontinence -associated dermatitis

Keep out of the reach of children

If swallowed get medical help or contact a poison control center right away

DOSAGE AND ADMINISTRATION

Gently cleanse and dry area. Apply as needed to affected area.

Inactive Ingredient:

Aloe Barbadensis Leaf Juice

Beeswax (Yellow Wax)

Disodium EDTA

DMDM Hydantoin

Lanolin Alcohol

Mineral Oil

Petrolatum

Sodium Borate

Sorbitan Sesquioleate

Water

WARNINGS

For external use only

When using this product, do not get into eyes

Stop use and ask doctor if condition lasts more than 7 days

Do not use on deep or punture wounds, animal bites, serious burns

Principal display Panel

NDC-68599-6202-1

McKesson

Skin Protectant Cream with Lanolin

Net Weight

0.18 oz (5 g)

MFR# 4613

PACKAGE LABEL

NDC-68599-6202-1

McKesson

Skin Protectant Cream with Lanolin

Net Weight

0.18 oz (5 g)

144 per Box

MFR# 4613

PACKAGE LABEL

NDC-68599-6202-1

McKesson

Skin Protectant Cream with Lanolin

Net Weight

0.18 oz (5 g)

MFR# 4613

Drug Facts

PACKAGE LABEL

NDC-68599-6202-4

McKesson

Skin Protectant Cream with Lanolin

Net Weight

0.18 oz (5 g)

2 per Case

MFR# 4613